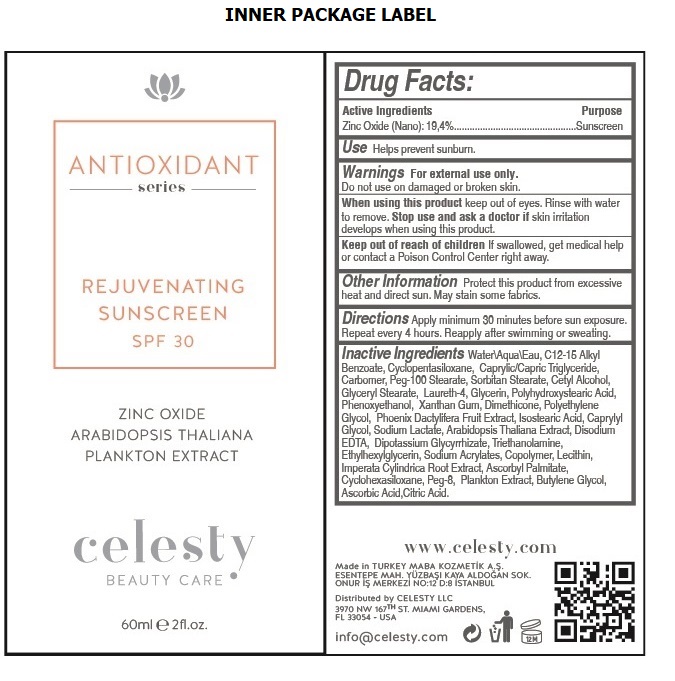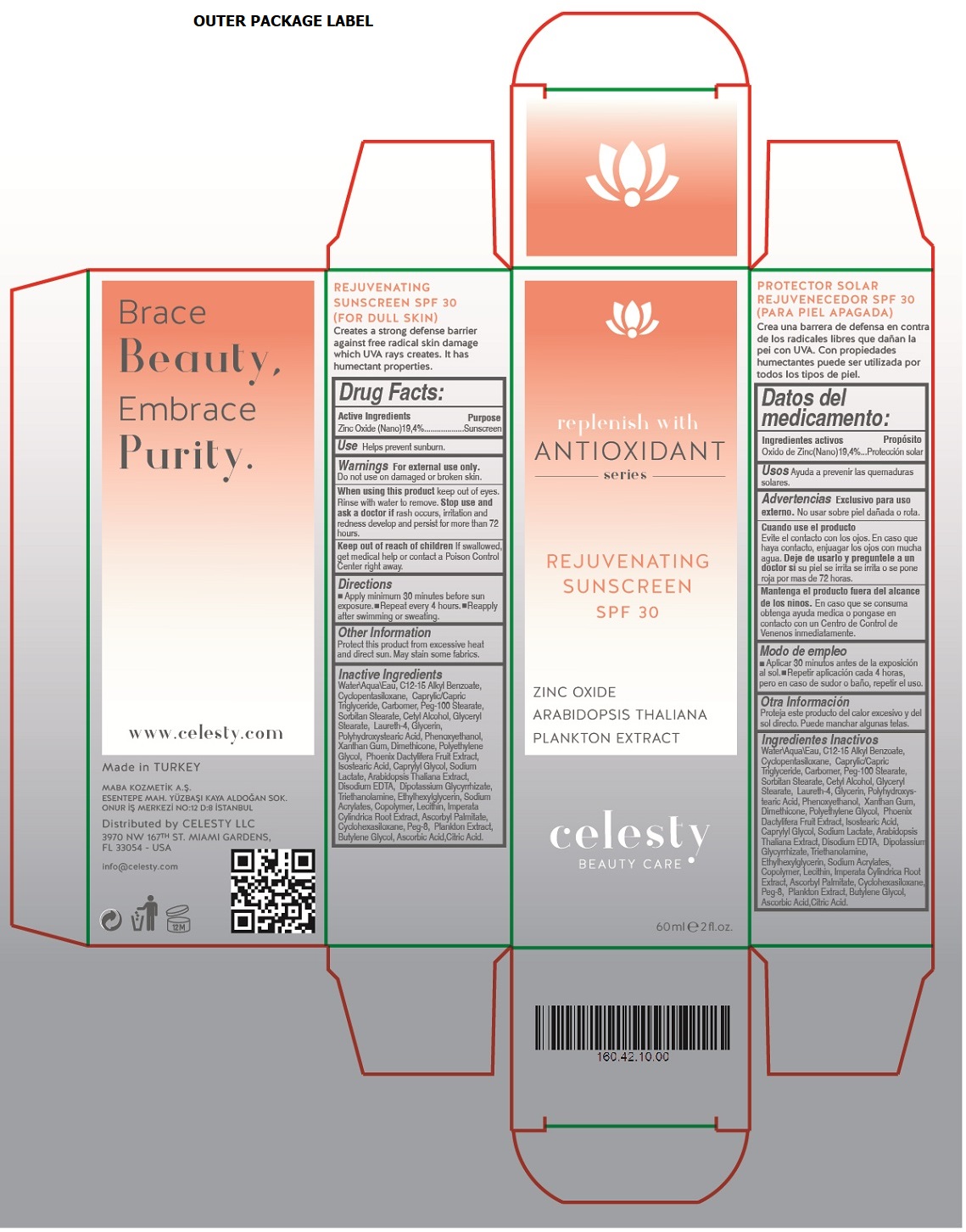 DRUG LABEL: Celesty
NDC: 81120-105 | Form: LOTION
Manufacturer: MABA KOZMETIK LIMITED SIRKETI
Category: otc | Type: HUMAN OTC DRUG LABEL
Date: 20201209

ACTIVE INGREDIENTS: ZINC OXIDE 194 mg/1 mL
INACTIVE INGREDIENTS: WATER; ALKYL (C12-15) BENZOATE; CYCLOMETHICONE 5; MEDIUM-CHAIN TRIGLYCERIDES; CARBOMER HOMOPOLYMER, UNSPECIFIED TYPE; PEG-100 STEARATE; SORBITAN MONOSTEARATE; CETYL ALCOHOL; GLYCERYL MONOSTEARATE; LAURETH-4; GLYCERIN; POLYHYDROXYSTEARIC ACID (2300 MW); PHENOXYETHANOL; XANTHAN GUM; DIMETHICONE; POLYETHYLENE GLYCOL, UNSPECIFIED; DATE; ISOSTEARIC ACID; CAPRYLYL GLYCOL; SODIUM LACTATE; ARABIDOPSIS THALIANA WHOLE; EDETATE DISODIUM ANHYDROUS; GLYCYRRHIZINATE DIPOTASSIUM; TROLAMINE; ETHYLHEXYLGLYCERIN; SODIUM POLYACRYLATE (2500000 MW); LECITHIN, SOYBEAN; IMPERATA CYLINDRICA ROOT; ASCORBYL PALMITATE; CYCLOMETHICONE 6; POLYETHYLENE GLYCOL 400; DIATOMACEOUS EARTH; BUTYLENE GLYCOL; ASCORBIC ACID; CITRIC ACID MONOHYDRATE

celesty ANTIOXIDANT series REJUVENATING SUNSCREEN SPF 30

Active Ingredients

Zinc Oxide (Nano) 19.4%

Purpose

Sunscreen

Use

Helps prevent sunburn.

Warnings

For external use only. Do not use on damaged or broken skin.

When using this product keep out of eyes. Rinse with water to remove. Stop use and ask a doctor if rash occurs, irritation and redness develop and persist for more than 72 hours.

Keep out of reach of children If swallowed, get medical help or contact a Poison Control Center right away.

Directions

• Apply minimum 30 minutes before sun exposure. • Repeat every 4 hours • Reapply after swimming or sweating.

Other Information

Protect this product from excessive heat and direct sun. May stain some fabrics.

Inactive Ingredients

Water\Aqua\Eau, C12-15 Alkyl Benzoate, Cyclopentasiloxane, Caprylic/Capric Triglyceride, Carbomer, Peg-100 Stearate, Sorbitan Stearate, Cetyl Alcohol, Glyceryl Stearate, Laureth-4, Glycerin, Polyhydroxystearic Acid, Phenoxyethanol, Xanthan Gum, Dimethicone, Polyethylene Glycol, Phoenix Dactylifera Fruit Extract, Isostearic Acid, Caprylyl Glycol, Sodium Lactate, Arabidopsis Thaliana Extract, Disodium EDTA, Dipotassium Glycyrrhizate, Triethanolamine, Ethylhexylglycerin, Sodium Acrylates Copolymer, Lecithin, Imperata Cylindrica Root Extract, Ascorbyl Palmitate, Cyclohexasiloxane, Peg-8, Plankton Extract, Butylene Glycol, Ascorbic Acid, Citric Acid

replenish with ANTIOXIDANT series

ZINC OXIDE

ARABIDOPSIS THALIANA

PLANKTON EXTRACT

BEAUTY CARE

Brace Beauty, Embrace Purity.

www.celesty.com

Made in TURKEY

MABA KOZMETIK A.S.

ESENTEPE MAH. YUZBASI KAYA ALDOGAN SOK.

ONUR IS MERKEZI NO:12 D:8 ISTANBUL

Distributed by CELESTY LLC

3970 NW 167TH ST. MIAMI GARDENS,

FL 33054 - USA

info@celesty.com

(FOR DULL SKIN)

Creates a strong defense barrier against free radical skin damage which UVA rays creates. It has humectant properties.